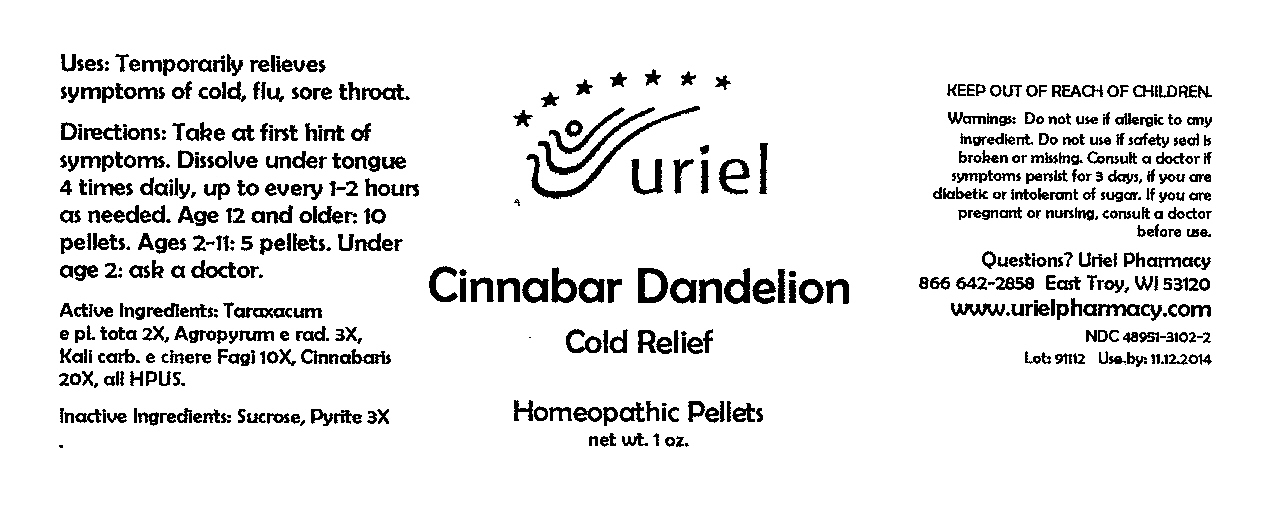 DRUG LABEL: Cinnabar Dandelion Cold Relief
NDC: 48951-3102 | Form: PELLET
Manufacturer: Uriel Pharmacy Inc
Category: homeopathic | Type: HUMAN OTC DRUG LABEL
Date: 20091231

ACTIVE INGREDIENTS: TARAXACUM OFFICINALE 2 [hp_X]/1 1; ELYMUS REPENS ROOT 3 [hp_X]/1 1; POTASH 10 [hp_X]/1 1; MERCURIC SULFIDE 20 [hp_X]/1 1
INACTIVE INGREDIENTS: SUCROSE

Cinnabar Dandelion Cold Relief Pellets - 1 oz.

Purpose

Uses: Temporarily relieves symptoms of cold, flu, sore throat.

Dosage & Administration

Directions: Take at first hint of symptoms. Dissolve under tongue. Take 4 times daily, up to every 1-2 hours as needed. Age 12 and older: 10 pellets. Ages 2-11: 5 pellets. Under age 2: ask a doctor.

OTC-Active Ingredient

Active Ingredients: Taraxacum e pl. tota 2X, Agropyrum e rad. 3X, Kali carb. e cinere Fagi 10X, Cinnabaris 20X, all HPUS.

Inactive Ingredient

Inactive Ingredient: Sucrose, Pyrite 3X.

Keep out of reach of children

Do not use section

Warnings:Do not use if allergic to any ingredient. Do not use if safety seal is broken or missing.

Ask doctor section

Consult a doctor if symptoms are serious or persist for 3 days, if you are diabetic or intolerant of sugar.

Pregnancy or breast feeding section

If you are pregnant or nursing, consult a doctor before use.

Questions section

Questions? Uriel Pharmacy

866 642-2858 East Troy, WI 53120

www.urielpharmacy.com

NDC 48951-3102-2

Principal Display Panel

Cinnabar Dandelion

Cold Relief

Homeopathic Pellets

net wt. 1 oz.